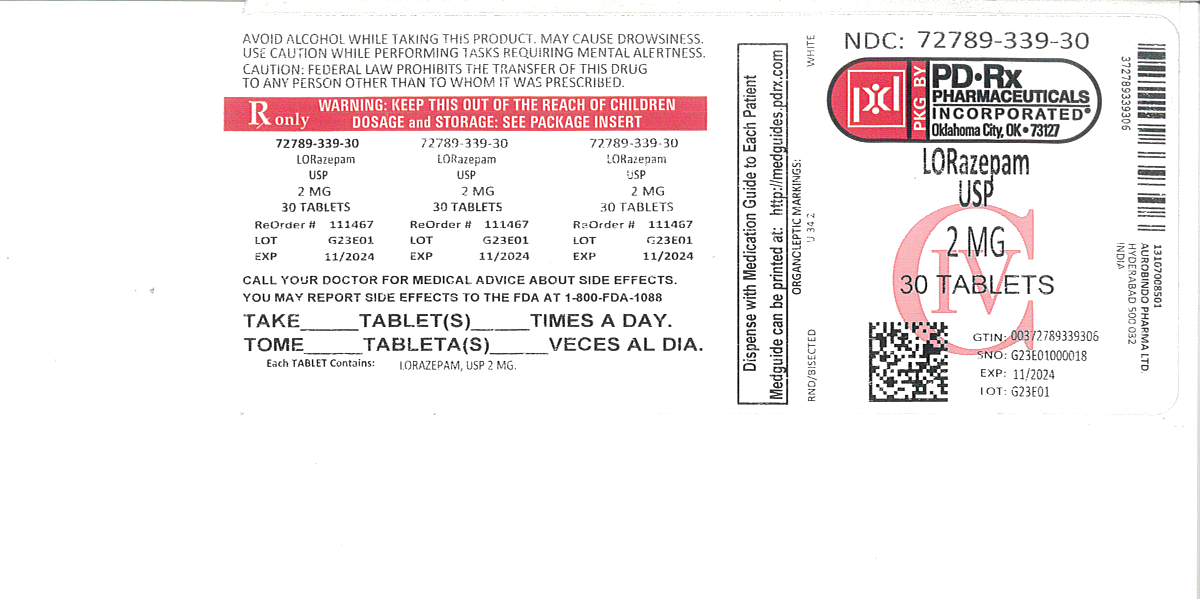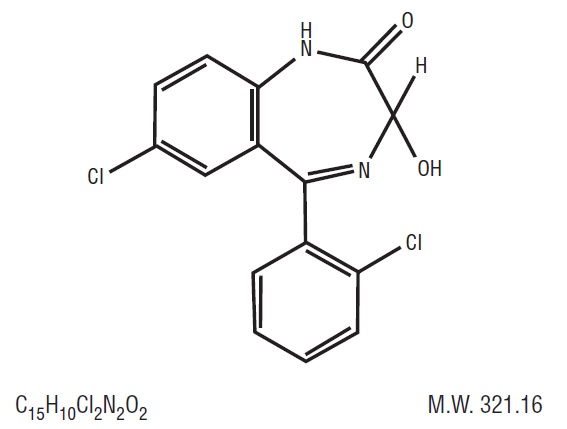 DRUG LABEL: LORAZEPAM
NDC: 72789-339 | Form: TABLET
Manufacturer: PD-Rx Pharmaceuticals, Inc.
Category: prescription | Type: HUMAN PRESCRIPTION DRUG LABEL
Date: 20260226
DEA Schedule: CIV

ACTIVE INGREDIENTS: LORAZEPAM 2 mg/1 1
INACTIVE INGREDIENTS: ANHYDROUS LACTOSE; MAGNESIUM STEARATE; CELLULOSE, MICROCRYSTALLINE; POLACRILIN POTASSIUM

Lorazepam Tablets, USP CIV
Rx only

WARNING: RISKS FROM CONCOMITANT USE WITH OPIOIDS; ABUSE, MISUSE, AND ADDICTION; and DEPENDENCE AND WITHDRAWAL REACTIONS

- Concomitant use of benzodiazepines and opioids may result in profound sedation, respiratory depression, coma, and death. Reserve concomitant prescribing of these drugs for patients for whom alternative treatment options are inadequate. Limit dosages and durations to the minimum required. Follow patients for signs and symptoms of respiratory depression and sedation (see WARNINGSand PRECAUTIONS).
- The use of benzodiazepines, including lorazepam, exposes users to risks of abuse, misuse, and addiction, which can lead to overdose or death. Abuse and misuse of benzodiazepines commonly involve concomitant use of other medications, alcohol, and/or illicit substances, which is associated with an increased frequency of serious adverse outcomes. Before prescribing lorazepam and throughout treatment, assess each patient’s risk for abuse, misuse, and addiction (see WARNINGS).
- The continued use of benzodiazepines, including lorazepam, may lead to clinically significant physical dependence. The risks of dependence and withdrawal increase with longer treatment duration and higher daily dose. Abrupt discontinuation or rapid dosage reduction of lorazepam after continued use may precipitate acute withdrawal reactions, which can be life-threatening. To reduce the risk of withdrawal reactions, use a gradual taper to discontinue lorazepam or reduce the dosage (DOSAGE AND ADMINISTRATIONand WARNINGS).

DESCRIPTION

Lorazepam USP,anantianxietyagent,has the chemicalformula,7-chloro-5-(o-chlorophenyl)-1,3-dihydro-3-hydroxy-2 H-1,4-benzodiazepin-2-one:
It is a nearlywhitepowderalmostinsoluble in water.Eachlorazepam tablet, USP to be takenorally,contains 0.5 mg, 1 mg, or 2 mg of lorazepam, USP. The inactiveingredientspresent are anhydrous lactose, magnesium stearate, microcrystalline cellulose, and polacrilin potassium.

CLINICAL PHARMACOLOGY

Studies in healthyvolunteersshowthat in singlehighdoseslorazepam has a tranquilizingaction on the centralnervoussystemwith no appreciableeffect on the respiratory or cardiovascularsystems.

Lorazepam is readilyabsorbedwithanabsolutebioavailability of 90%.Peakconcentrations in plasmaoccurapproximately 2 hoursfollowingadministration. The peakplasmalevel of lorazepam from a 2 mgdose is approximately 20 ng/mL.

The meanhalf-life of unconjugatedlorazepam inhumanplasma is about 12 hoursand for its majormetabolite,lorazepam glucuronide,about 18 hours.Atclinicallyrelevantconcentrations,lorazepam isapproximately 85% bound to plasmaproteins.Lorazepam is rapidlyconjugatedatits3-hydroxy group into lorazepam glucuronidewhich is thenexcreted in the urine. Lorazepam glucuronidehas no demonstrablecentralnervoussystem(CNS)activityinanimals.

The plasmalevels of lorazepam areproportionaltothedosegiven. There is no evidence of accumulation of lorazepam onadministrationup to 6 months.

Studiescomparing young andelderlysubjectshaveshownthatadvancingagedoes not have a significanteffect on the pharmacokinetics of lorazepam.However, in one studyinvolvingsingleintravenousdoses of 1.5 to 3 mg of lorazepam Injection,meantotalbodyclearance of lorazepam decreasedby20% in 15 elderlysubjects of 60 to 84 years of agecompared to that in 15youngersubjects of 19 to 38 years of age.

INDICATIONS AND USAGE

Lorazepam tablets areindicated for the management of anxietydisorders or for theshort-termrelief of the symptoms of anxiety or anxietyassociatedwithdepressivesymptoms.Anxiety or tensionassociatedwith the stress of everyday life usuallydoesnotrequiretreatmentwith an anxiolytic.

The effectiveness of lorazepam tablets in long-termuse,thatis,morethan 4 months,has not been assessed by systematicclinicalstudies. The physicianshouldperiodicallyreassess the usefulness of the drug for the individualpatient.

CONTRAINDICATIONS

Lorazepam is contraindicated in patientswith:

- hypersensitivity to benzodiazepines or to anycomponents of the formulation
- acutenarrow-angleglaucoma.

WARNINGS

Risks from Concomitant Use with Opioids

Concomitantuse of benzodiazepines, including lorazepam,andopioidsmayresult in profoundsedation,respiratorydepression,coma,anddeath.Because of theserisks,reserveconcomitantprescribing of these drugs in patients for whomalternativetreatmentoptionsareinadequate.

Observationalstudieshavedemonstratedthatconcomitantuse of opioid analgesicsandbenzodiazepinesincreases the risk of drug-relatedmortalitycompared to use of opioidsalone. If a decision is made to prescribelorazepam concomitantlywithopioids,prescribe the lowesteffectivedosagesandminimumdurations of concomitantuse,andfollowpatientsclosely for signsandsymptoms of respiratorydepression andsedation. In patientsalreadyreceivinganopioidanalgesic,prescribe a lowerinitialdose of lorazepam thanindicated in theabsence of anopioidandtitratebased on clinicalresponse. If an opioid is initiated in a patientalreadytakinglorazepam,prescribe a lowerinitialdose of the opioidandtitratebased upon clinicalresponse.

Advise both patientsandcaregiversabout the risks of respiratorydepressionandsedationwhenlorazepam is usedwithopioids.Advisepatients not to drive or operateheavymachineryuntil the effects of concomitantusewith the opioidhavebeendetermined(see PRECAUTIONS: Drug Interactions).

Abuse, Misuse, and Addiction

The use of benzodiazepines, including lorazepam, exposes users to the risks of abuse, misuse, and addiction, which can lead to overdose or death. Abuse and misuse of benzodiazepines often (but not always) involve the use of doses greater than the maximum recommended dosage and commonly involve concomitant use of other medications, alcohol, and/or illicit substances, which is associated with an increased frequency of serious adverse outcomes, including respiratory depression, overdose, or death (see DRUG ABUSE AND DEPENDENCE: Abuse).

Before prescribing lorazepam and throughout treatment, assess each patient’s risk for abuse, misuse, and addiction (e.g., using a standardized screening tool). Use of lorazepam, particularly in patients at elevated risk, necessitates counseling about the risks and proper use of lorazepam along with monitoring for signs and symptoms of abuse, misuse, and addiction. Prescribe the lowest effective dosage; avoid or minimize concomitant use of CNS depressants and other substances associated with abuse, misuse, and addiction (e.g., opioid analgesics, stimulants); and advise patients on the proper disposal of unused drug. If a substance use disorder is suspected, evaluate the patient and institute (or refer them for) early treatment, as appropriate.

Dependence and Withdrawal Reactions

To reduce the risk of withdrawal reactions, use a gradual taper to discontinue lorazepam or reduce the dosage (a patient-specific plan should be used to taper the dose) (see DOSAGE AND ADMINISTRATION: Discontinuation or Dosage Reduction of lorazepam).

Patients at an increased risk of withdrawal adverse reactions after benzodiazepine discontinuation or rapid dosage reduction include those who take higher dosages, and those who have had longer durations of use.

Acute Withdrawal Reactions

The continued use of benzodiazepines, including lorazepam, may lead to clinically significant physical dependence. Abrupt discontinuation or rapid dosage reduction of lorazepam after continued use, or administration of flumazenil (a benzodiazepine antagonist) may precipitate acute withdrawal reactions, which can be life-threatening (e.g., seizures) (see DRUG ABUSE AND DEPENDENCE: Dependence).

Protracted Withdrawal Syndrome

In some cases, benzodiazepine users have developed a protracted withdrawal syndrome with withdrawal symptoms lasting weeks to more than 12 months (see DRUG ABUSE AND DEPENDENCE: Dependence).

Pre-existing depression may emerge or worsen during use of benzodiazepines including lorazepam. Lorazepam is not recommended for use in patients with a primary depressive disorder or psychosis.

Use of benzodiazepines, including lorazepam, both used alone and in combination with other CNS depressants, may lead to potentially fatal respiratory depression (see PRECAUTIONS: Drug Interactions).

As with all patients on CNS-depressant drugs, patients receiving lorazepam should be warned not to operate dangerous machinery or motor vehicles and that their tolerance for alcohol and other CNS depressants will be diminished.

Neonatal Sedation and Withdrawal Syndrome

Use of lorazepam late in pregnancy can result in sedation (respiratory depression, lethargy, hypotonia) and/or withdrawal symptoms (hyperreflexia, irritability, restlessness, tremors, inconsolable crying, and feeding difficulties) in the neonate (see PRECAUTIONS: Pregnancy). Monitor neonates exposed to lorazepam during pregnancy or labor for signs of sedation and monitor neonates exposed to lorazepam during pregnancy for signs of withdrawal; manage these neonates accordingly.

PRECAUTIONS

In patientswithdepression, a possibility for suicideshould be borne in mind;benzodiazepinesshould not be used in suchpatientswithoutadequateantidepressanttherapy.

Lorazepam should be usedwithcaution in patientswithcompromisedrespiratoryfunction(e.g.,COPD,sleepapneasyndrome).

Elderly or debilitatedpatientsmay be moresusceptible to the sedativeeffects of lorazepam.Therefore,thesepatientsshould be monitoredfrequentlyandhavetheirdosageadjustedcarefullyaccordingto patientresponse; the initialdosageshould not exceed 2 mg.

Paradoxicalreactionshavebeenoccasionallyreportedduringbenzodiazepineuse.Suchreactionsmay be morelikelytooccur in childrenand the elderly.Shouldtheseoccur,use of the drugshould be discontinued.

The usualprecautions for treatingpatientswithimpairedrenal or hepaticfunctionshould be observed.As withallbenzodiazepines, the use of lorazepam mayworsenhepaticencephalopathy;therefore,lorazepam should be usedwithcaution in patientswithseverehepaticinsufficiencyand/orencephalopathy.Dosage for patientswithseverehepaticinsufficiencyshould be adjustedcarefullyaccording to patientresponse;lowerdosesmay be sufficient in suchpatients.

In patientswheregastrointestinal or cardiovasculardisorderscoexistwithanxiety, it shouldbenotedthat lorazepam has not beenshown to be of significantbenefit in treating the gastrointestinal or cardiovascular component.

Esophagealdilationoccurred in ratstreatedwithlorazepam formorethan 1 yearat 6 mg/kg/day. The no-effectdose was 1.25 mg/kg/day(approximately 6 times the maximumhumantherapeuticdose of 10 mg/day). The effect was reversibleonlywhen the treatmentwaswithdrawnwithin 2 months of first observationof the phenomenon. The clinicalsignificance of this is unknown.However,use of lorazepam forprolongedperiodsandingeriatricpatientsrequirescaution,andthereshould be frequentmonitoring for symptoms of upperGIdisease.

Safetyandeffectiveness of lorazepam in children of lessthan 12 yearshave not beenestablished.

Information for Patients

Advise the patient to read the FDA-approved patient labeling (Medication Guide).

Risks from Concomitant Use with Opioids

Advise both patients and caregivers about the risks of potentially fatal respiratory depression and sedation when lorazepam is used with opioids and not to use such drugs concomitantly unless supervised by a healthcare provider. Advise patients not to drive or operate heavy machinery until the effects of concomitant use with the opioid have been determined (see WARNINGS: Risks from Concomitant Use of Opioids and PRECAUTIONS: Drug Interactions).

Abuse, Misuse, and Addiction

Inform patients that the use of lorazepam even at recommended doses, exposes users to risks of abuse, misuse, and addiction, which can lead to overdose and death, especially when used in combination with other medications (e.g., opioid analgesics), alcohol, and/or illicit substances. Inform patients about the signs and symptoms of benzodiazepine abuse, misuse, and addiction; to seek medical help if they develop these signs and/or symptoms; and on the proper disposal of unused drug (see WARNINGS: Abuse Misuse, and Addiction and DRUG ABUSE AND DEPENDENCE).

Withdrawal Reactions

Inform patients that the continued use of lorazepam may lead to clinically significant physical dependence and that abrupt discontinuation or rapid dosage reduction of lorazepam may precipitate acute withdrawal reactions, which can be life-threatening. Inform patients that in some cases, patients taking benzodiazepines have developed a protracted withdrawal syndrome with withdrawal symptoms lasting weeks to more than 12 months. Instruct patients that discontinuation or dosage reduction of lorazepam may require a slow taper (see WARNINGS: Dependence and Withdrawal Reactions and DRUG ABUSE AND DEPENDENCE).

Pregnancy

Advise pregnant females that use of lorazepam late in pregnancy can result in sedation (respiratory depression, lethargy, hypotonia) and/or withdrawal symptoms (hyperreflexia, irritability, restlessness, tremors, inconsolable crying, and feeding difficulties) in newborns (see WARNINGS: Neonatal Sedation and Withdrawal Syndrome and PRECAUTIONS: Pregnancy). Instruct patients to inform their healthcare provider if they are pregnant.

Advise patients that there is a pregnancy exposure registry that monitors pregnancy outcomes in women exposed to lorazepam during pregnancy (see PRECAUTIONS: Pregnancy).

Nursing

Instruct patients to notify their healthcare provider if they are breastfeeding or intend to breastfeed. Instruct breastfeeding patients using lorazepam to monitor infants for excessive sedation, poor feeding and poor weight gain, and to seek medical attention if they notice these signs (see PRECAUTIONS: Nursing Mothers).

Essential Laboratory Tests

Some patients on lorazepam have developed leukopenia, and some have had elevations of LDH. As with other benzodiazepines, periodic blood counts and liver function tests are recommended for patients on long-term therapy.

Drug Interactions

The concomitant use of benzodiazepines and opioids increases the risk of respiratory depression because of actions at different receptor sites in the CNS that control respiration. Benzodiazepines interact at GABAAsites and opioids interact primarily at mu receptors. When benzodiazepines and opioids are combined, the potential for benzodiazepines to significantly worsen opioid-related respiratory depression exists. Limit dosage and duration of concomitant use of benzodiazepines and opioids, and monitor patients closely for respiratory depression and sedation.

The benzodiazepines, including lorazepam, produce increased CNS-depressant effects when administered with other CNS depressants such as alcohol, barbiturates, antipsychotics, sedative/hypnotics, anxiolytics, antidepressants, narcotic analgesics, sedative antihistamines, anticonvulsants, and anesthetics.

Concomitant use of clozapine and lorazepam may produce marked sedation, excessive salivation, hypotension, ataxia, delirium, and respiratory arrest.

Concurrent administration of lorazepam with valproate results in increased plasma concentrations and reduced clearance of lorazepam. Lorazepam dosage should be reduced to approximately 50% when coadministered with valproate.

Concurrent administration of lorazepam with probenecid may result in a more rapid onset or prolonged effect of lorazepam due to increased half-life and decreased total clearance. Lorazepam dosage needs to be reduced by approximately 50% when coadministered with probenecid.

The effects of probenecid and valproate on lorazepam may be due to inhibition of glucuronidation.

Administration of theophylline or aminophylline may reduce the sedative effects of benzodiazepines, including lorazepam.

Carcinogenesis and Mutagenesis

No evidence of carcinogenic potential emerged in rats during an 18-month study with lorazepam. No studies regarding mutagenesis have been performed.

Pregnancy

Pregnancy Exposure Registry

There is a pregnancy registry that monitors pregnancy outcomes in women exposed to psychiatric medications, including lorazepam, during pregnancy. Healthcare providers are encouraged to register patients by calling the National Pregnancy Registry for Psychiatric Medications at 1-866-961-2388 or visiting online at https://womensmentalhealth.org/pregnancyregistry/.

Risk Summary

Neonates born to mothers using benzodiazepines late in pregnancy have been reported to experience symptoms of sedation and/or neonatal withdrawal (see WARNINGS: Neonatal Sedation and Withdrawal Syndrome and Clinical Considerations). Available data from published observational studies of pregnant women exposed to benzodiazepines do not report a clear association with benzodiazepines and major birth defects (see Data).

The background risk of major birth defects and miscarriage for the indicated population is unknown. All pregnancies have a background risk of birth defect, loss, or other adverse outcomes. In the U.S. general population, the estimated risk of major birth defects and of miscarriage in clinically recognized pregnancies is 2% to 4% and 15% to 20%, respectively.

Clinical Considerations

Fetal/Neonatal Adverse Reactions

Benzodiazepines cross the placenta and may produce respiratory depression, hypotonia and sedation in neonates. Monitor neonates exposed to lorazepam during pregnancy or labor for signs of sedation, respiratory depression, hypotonia, and feeding problems. Monitor neonates exposed to lorazepam during pregnancy for signs of withdrawal. Manage these neonates accordingly (see WARNINGS: Neonatal Sedation and Withdrawal Syndrome).

Data

Human Data

Published data from observational studies on the use of benzodiazepines during pregnancy do not report a clear association with benzodiazepines and major birth defects. Although early studies reported an increased risk of congenital malformations with diazepam and chlordiazepoxide, there was no consistent pattern noted. In addition, the majority of more recent case-control and cohort studies of benzodiazepine use during pregnancy, which were adjusted for confounding exposures to alcohol, tobacco and other medications, have not confirmed these findings.

Animal Data

Reproductive studies in animals were performed in mice, rats, and two strains of rabbits. Occasional anomalies (reduction of tarsals, tibia, metatarsals, malrotated limbs, gastroschisis, malformed skull, and microphthalmia) were seen in drug-treated rabbits without relationship to dosage. Although all of these anomalies were not present in the concurrent control group, they have been reported to occur randomly in historical controls. At doses of 40 mg/kg and higher, there was evidence of fetal resorption and increased fetal loss in rabbits which was not seen at lower doses.

Nursing Mothers

Risk Summary

Lorazepam is present in breast milk. There are reports of sedation, poor feeding and poor weight gain in infants exposed to benzodiazepines through breast milk. The effects of lorazepam on milk production are unknown. The developmental and health benefits of breastfeeding should be considered along with the mother’s clinical need for lorazepam and any potential adverse effects on the breastfed infant from lorazepam or from the underlying maternal condition.

Clinical Considerations

Infants exposed to lorazepam through breast milk should be monitored for sedation, poor feeding and poor weight gain.

Geriatric Use

Clinical studies of lorazepam generally were not adequate to determine whether subjects aged 65 and over respond differently than younger subjects; however, the incidence of sedation and unsteadiness was observed to increase with age (see ADVERSE REACTIONS).

Age does not appear to have a significant effect on lorazepam kinetics (see CLINICAL PHARMACOLOGY).

Clinical circumstances, some of which may be more common in the elderly, such as hepatic or renal impairment, should be considered. Greater sensitivity (e.g., sedation) of some older individuals cannot be ruled out. In general, dose selection for an elderly patient should be cautious, and lower doses may be sufficient in these patients (see DOSAGE AND ADMINISTRATION).

ADVERSE REACTIONS

Mostadversereactions to benzodiazepines,includingCNSeffectsandrespiratorydepression,aredose dependent,withmoresevereeffectsoccurringwithhighdoses.

In a sample of about3500patientstreated for anxiety, the mostfrequentadversereaction to lorazepam wassedation(15.9%),followedbydizziness(6.9%),weakness(4.2%),andunsteadiness(3.4%). The incidence of sedationandunsteadinessincreasedwithage.

Otheradversereactions to benzodiazepines,includinglorazepam arefatigue,drowsiness,amnesia,memoryimpairment,confusion,disorientation,depression,unmasking of depression,disinhibition,euphoria,suicidalideation/attempt,ataxia,asthenia,extrapyramidalsymptoms,convulsions/seizures,tremor,vertigo,eyefunction/visualdisturbance(includingdiplopiaandblurredvision),dysarthria/slurred speech,change in libido,impotence,decreasedorgasm;headache,coma;respiratorydepression,apnea,worsening of sleepapnea,worsening of obstructivepulmonarydisease;gastrointestinalsymptoms includingnausea,change in appetite,constipation,jaundice,increase in bilirubin,increase in liver transaminases,increase in alkalinephosphatase;hypersensitivityreactions,anaphylactoidreactions;dermatologicalsymptoms,allergicskinreactions,alopecia;syndrome of inappropriateantidiuretic hormone(SIADH),hyponatremia;thrombocytopenia,agranulocytosis,pancytopenia;hypothermia;andautonomicmanifestations.

Paradoxicalreactions,includinganxiety,excitation,agitation,hostility,aggression,rage,sleepdisturbances/insomnia,sexualarousal,andhallucinationsmayoccur.Small decreases in blood pressure andhypotensionmayoccur but areusually not clinicallysignificant,probablybeingrelated to therelief of anxietyproducedbylorazepam.
To report SUSPECTED ADVERSE REACTIONS, contact Aurobindo Pharma USA, Inc. at 1-866-850-2876 or FDA at 1-800-FDA-1088 or www.fda.gov/medwatch.

DRUG ABUSE AND DEPENDENCE

Controlled Substance

Lorazepam tablets contains lorazepam, a Schedule IV controlled substance.

Abuse

Lorazepam is a benzodiazepine and a CNS depressant with a potential for abuse and addiction. Abuse is the intentional, non-therapeutic use of a drug, even once, for its desirable psychological or physiological effects. Misuse is the intentional use, for therapeutic purposes, of a drug by an individual in a way other than prescribed by a healthcare provider or for whom it was not prescribed. Drug addiction is a cluster of behavioral, cognitive, and physiological phenomena that may include a strong desire to take the drug, difficulties in controlling drug use (e.g., continuing drug use despite harmful consequences, giving a higher priority to drug use than other activities and obligations), and possible tolerance or physical dependence. Even taking benzodiazepines as prescribed may put patients at risk for abuse and misuse of their medication. Abuse and misuse of benzodiazepines may lead to addiction.

Abuse and misuse of benzodiazepines often (but not always) involve the use of doses greater than the maximum recommended dosage and commonly involve concomitant use of other medications, alcohol, and/or illicit substances, which is associated with an increased frequency of serious adverse outcomes, including respiratory depression, overdose, or death. Benzodiazepines are often sought by individuals who abuse drugs and other substances, and by individuals with addictive disorders (see WARNINGS: Abuse, Misuse, and Addiction).

The following adverse reactions have occurred with benzodiazepine abuse and/or misuse: abdominal pain, amnesia, anorexia, anxiety, aggression, ataxia, blurred vision, confusion, depression, disinhibition, disorientation, dizziness, euphoria, impaired concentration and memory, indigestion, irritability, muscle pain, slurred speech, tremors, and vertigo.

The following severe adverse reactions have occurred with benzodiazepine abuse and/or misuse: delirium, paranoia, suicidal ideation and behavior, seizures, coma, breathing difficulty, and death. Death is more often associated with polysubstance use (especially benzodiazepines with other CNS depressants such as opioids and alcohol).

Dependence

Physical Dependence

Lorazepam may produce physical dependence from continued therapy. Physical dependence is a state that develops as a result of physiological adaptation in response to repeated drug use, manifested by withdrawal signs and symptoms after abrupt discontinuation or a significant dose reduction of a drug. Abrupt discontinuation or rapid dosage reduction of benzodiazepines or administration of flumazenil, a benzodiazepine antagonist, may precipitate acute withdrawal reactions, including seizures, which can be life-threatening. Patients at an increased risk of withdrawal adverse reactions after benzodiazepine discontinuation or rapid dosage reduction include those who take higher dosages (i.e., higher and/or more frequent doses) and those who have had longer durations of use (see WARNINGS: Dependence and Withdrawal Reactions).

To reduce the risk of withdrawal reactions, use a gradual taper to discontinue lorazepam or reduce the dosage (see DOSAGE AND ADMINISTRATION: Discontinuation or Dosage Reduction of lorazepam and WARNINGS).

Acute Withdrawal Signs and Symptoms

Acute withdrawal signs and symptoms associated with benzodiazepines have included abnormal involuntary movements, anxiety, blurred vision, depersonalization, depression, derealization, dizziness, fatigue, gastrointestinal adverse reactions (e.g., nausea, vomiting, diarrhea, weight loss, decreased appetite), headache, hyperacusis, hypertension, irritability, insomnia, memory impairment, muscle pain and stiffness, panic attacks, photophobia, restlessness, tachycardia, and tremor. More severe acute withdrawal signs and symptoms, including life-threatening reactions, have included catatonia, convulsions, delirium tremens, depression, hallucinations, mania, psychosis, seizures and suicidality.

Protracted Withdrawal Syndrome

Protracted withdrawal syndrome associated with benzodiazepines is characterized by anxiety, cognitive impairment, depression, insomnia, formication, motor symptoms (e.g., weakness, tremor, muscle twitches), paresthesia, and tinnitus that persists beyond 4 to 6 weeks after initial benzodiazepine withdrawal. Protracted withdrawal symptoms may last weeks to more than 12 months. As a result, there may be difficulty in differentiating withdrawal symptoms from potential re-emergence or continuation of symptoms for which the benzodiazepine was being used.

Tolerance

Tolerance to lorazepam may develop from continued therapy. Tolerance is a physiological state characterized by a reduced response to a drug after repeated administration (i.e., a higher dose of a drug is required to produce the same effect that was once obtained at a lower dose). Tolerance to the therapeutic effect of lorazepam may develop; however, little tolerance develops to the amnestic reactions and other cognitive impairments caused by benzodiazepines.

OVERDOSAGE

Overdosage of benzodiazepines is characterized by central nervous system depression ranging from drowsiness to coma. In mild to moderate cases, symptoms can include drowsiness, confusion, dysarthria, lethargy, hypnotic state, diminished reflexes, ataxia, and hypotonia. Rarely, paradoxical or disinhibitory reactions (including agitation, irritability, impulsivity, violent behavior, confusion, restlessness, excitement, and talkativeness) may occur. In severe overdosage cases, patients may develop respiratory depression and coma. Overdosage of benzodiazepines in combination with other CNS depressants (including alcohol and opioids) may be fatal (see WARNINGS: Abuse, Misuse , and Addiction). Markedly abnormal (lowered or elevated) blood pressure, heart rate, or respiratory rate raise the concern that additional drugs and/or alcohol are involved in the overdosage.

In managing benzodiazepine overdosage, employ general supportive measures, including intravenous fluids and airway management. Flumazenil, a specific benzodiazepine receptor antagonist indicated for the complete or partial reversal of the sedative effects of benzodiazepines in the management of benzodiazepine overdosage, can lead to withdrawal and adverse reactions, including seizures, particularly in the context of mixed overdosage with drugs that increase seizure risk (e.g., tricyclic and tetracyclic antidepressants) and in patients with long-term benzodiazepine use and physical dependency. The risk of withdrawal seizures with flumazenil use may be increased in patients with epilepsy. Flumazenil is contraindicated in patients who have received a benzodiazepine for control of a potentially life-threatening condition (e.g., status epilepticus). If the decision is made to use flumazenil, it should be used as an adjunct to, not as a substitute for, supportive management of benzodiazepine overdosage. See the flumazenil injection Prescribing Information.

Consider contacting the Poison Help line (1-800-222-1222) or a medical toxicologist for additional overdosage management recommendations.

DOSAGE AND ADMINISTRATION

Lorazepam tablets are administeredorally. For optimalresults,dose,frequency of administration,andduration of therapyshould be individualizedaccording to patientresponse. To facilitatethis,0.5mg, 1 mg,and 2 mgtabletsareavailable.

The usualrange is 2 to 6 mg/daygivenindivideddoses, the largestdosebeingtakenbeforebedtime, but the dailydosagemayvaryfrom 1 to 10 mg/day.

For anxiety,mostpatientsrequireaninitialdose of 2 to 3 mg/daygiventwotimes a day or threetimes a day.

For insomnia due to anxiety or transientsituationalstress, a singledailydose of 2 to 4 mgmay be given,usuallyatbedtime.

For elderly or debilitatedpatients,aninitialdosage of 1 to 2 mg/day in divideddoses is recommended, to be adjustedasneededandtolerated.

The dosageoflorazepam tablets should be increasedgraduallywhenneeded to helpavoidadverse effects.Whenhigherdosage is indicated, the eveningdoseshouldbeincreasedbefore the daytimedoses.

Discontinuation or Dosage Reduction of Lorazepam Tablets

To reduce the risk of withdrawal reactions, use a gradual taper to discontinue lorazepam tablets or reduce the dosage. If a patient develops withdrawal reactions, consider pausing the taper or increasing the dosage to the previous tapered dosage level. Subsequently decrease the dosage more slowly (see WARNINGS: Dependence and Withdrawal Reactions and DRUG ABUSE AND DEPENDENCE: Dependence).

HOW SUPPLIED

Lorazepam Tablets, USP are available in the following dosage strengths:

2 mg, white to off-white, round, flat-faced beveled edge tablets debossed with a bisect separating “U” and “34” on one side and “2” on other side.

Bottles of 30 tablets NDC 72789-339-30

Keep bottles tightly closed.

Keep out of reach of children.
Store at 20° to 25°C (68° to 77°F). [See USP Controlled Room Temperature].
Dispense in a tight, light-resistant container as described in the USP.
Dispense with Medication Guide available at: www.aurobindousa.com/medication-guides

MEDICATION GUIDE
Lorazepam Tablets, USP CIV
(lor-A-ze-pam)

What is the most important information I should know about lorazepam tablets?

- Lorazepam tablets are a benzodiazepine medicine. Taking benzodiazepines with opioid medicines, alcohol, or other central nervous system depressants (including street drugs) can cause severe drowsiness, breathing problems (respiratory depression), coma and death.Get emergency help right away if any of the following happens:
  - shallow or slowed breathing
  - breathing stops (which may lead to the heart stopping)
  - excessive sleepiness (sedation)

Do not drive or operate heavy machinery until you know how taking lorazepam tablets with opioids affects you.

- Risk of abuse, misuse, and addiction.There is a risk of abuse, misuse, and addiction with benzodiazepines including lorazepam tablets which can lead to overdose and serious side effects including coma and death.
  - Serious side effects including coma and death have happened in people who have abused or misused benzodiazepines, including lorazepam tablets.These serious side effects may also include delirium, paranoia, suicidal thoughts or actions, seizures, and difficulty breathing. Call your healthcare provider or go to the nearest hospital emergency room right away if you get any of these serious side effects.
  - You can develop an addiction even if you take lorazepam tablets exactly as prescribed by your healthcare provider.
  - Take lorazepam tablets exactly as your healthcare provider prescribed.
  - Do not share your lorazepam tablets with other people.
  - Keep lorazepam tablets in a safe place and away from children.
- Physical dependence and withdrawal reactions.Lorazepam tablets can cause physical dependence and withdrawal reactions.
  - Do not suddenly stop taking lorazepam tablets.Stopping lorazepam tablets suddenly can cause serious and life-threatening side effects, including, unusual movements, responses or expressions, seizures, sudden and severe mental or nervous system changes, depression, seeing or hearing things that others do not see or hear, an extreme increase in activity or talking, losing touch with reality, and suicidal thoughts or actions. Call your healthcare provider or go to the nearest hospital emergency room right away if you get any of these symptoms.
  - Some people who suddenly stop benzodiazepines have symptoms that can last for several weeks to more than 12 months,including anxiety, trouble remembering, learning, or concentrating, depression, problems sleeping, feeling like insects are crawling under your skin, weakness, shaking, muscle twitching, burning or prickling feeling in your hands, arms, legs or feet, and ringing in your ears.
  - Physical dependence is not the same as drug addiction. Your healthcare provider can tell you more about the differences between physical dependence and drug addiction.
  - Do not take more lorazepam tablets than prescribed or take lorazepam tablets for longer than prescribed.

What are lorazepam tablets?

- Lorazepam tablets are a prescription medicine used:
  - to treat anxiety disorders
  - for the short-term relief of the symptoms of anxiety or anxiety that can happen with symptoms of depression
  - Lorazepam tablets are a federal controlled substance (CIV) because it contains lorazepam that can be abused or lead to dependence.Keep lorazepam tablets in a safe place to prevent misuse and abuse. Selling or giving away lorazepam tablets may harm others, and is against the law. Tell your healthcare provider if you have abused or been dependent on alcohol, prescription medicines or street drugs.
  - It is not known if lorazepam tablets are safe and effective for use in children less than 12 years of age.
  - It is not known if lorazepam tablets are safe and effective for use for longer than 4 months.

Do not take lorazepam tablets if you:

- are allergic to lorazepam, other benzodiazepines, or any of the ingredients in lorazepam tablets. See the end of this Medication Guide for a complete list of ingredients in lorazepam tablets.

Before you take lorazepam tablets, tell your healthcare provider about all of your medical conditions, including if you:

- have or have had depression, mood problems, or suicidal thoughts or behavior
- have a history of drug or alcohol abuse or addiction
- have lung disease or breathing problems (such as COPD, sleep apnea syndrome)
- have liver or kidney problems
- have or have had seizures
- are pregnant or plan to become pregnant.
  - Taking lorazepam tablets late in pregnancy may cause your baby to have symptoms of sedation (breathing problems, sluggishness, low muscle tone), and/or withdrawal symptoms (jitteriness, irritability, restlessness, shaking, excessive crying, feeding problems).
  - Tell your healthcare provider right away if you become pregnant or think you are pregnant during treatment with lorazepam tablets.
  - There is a pregnancy registry for women who take lorazepam tablets during pregnancy. The purpose of the registry is to collect information about the health of you and your baby. If you become pregnant during treatment with lorazepam tablets, talk to your healthcare provider about registering with the National Pregnancy Registry for Psychiatric Medications. You can register by calling 1-866-961-2388 or visiting https://womensmentalhealth.org/pregnancyregistry/.
- are breastfeeding or plan to breastfeed. Lorazepam passes into your breast milk.
  - Breastfeeding during treatment with lorazepam tablets may cause your baby to have sleepiness, feeding problems, and decreased weight gain.
  - Talk to your healthcare provider about the best way to feed your baby if you take lorazepam tablets.

Tell your healthcare provider about all the medicines you take, including prescription and over-the-counter medicines, vitamins, and herbal supplements.
Taking lorazepam tablets with certain other medicines can cause side effects or affect how well lorazepam tablets or the other medicines work. Do not start or stop other medicines without talking to your healthcare provider.

How should I take lorazepam tablets?

- Take lorazepam tablets exactly as your healthcare provider tells you to take it. Your healthcare provider will tell you how much lorazepam tablets to take and when to take it.
- If you take too much lorazepam tablets, call your healthcare provider or go to the nearest hospital emergency room right away.

What are the possible side effects of lorazepam tablets?
Lorazepam tablets may cause serious side effects, including:

- See “What is the most important information I should know about lorazepam tablets?”
- Lorazepam tablets can make you sleepy or dizzy and can slow your thinking and motor skills.
  - Do not drive, operate heavy machinery, or do other dangerous activities until you know how lorazepam tablets affects you.
  - Do not drink alcohol or take other drugs that may make you sleepy or dizzy while taking lorazepam tablets without first talking to your healthcare provider.When taken with alcohol or drugs that cause sleepiness or dizziness, lorazepam tablets may make your sleepiness or dizziness much worse.
- Depression.Pre-existing depression may emerge or worsen during use of benzodiazepines including lorazepam tablets.

The most common side effects of lorazepam tablets include:
• sedation • dizziness
• weakness • unsteadiness
These are not all the possible side effects of lorazepam tablets. Call your doctor for medical advice about side effects. You may report side effects to FDA at 1-800-FDA-1088.

How should I store lorazepam tablets?

- Store lorazepam tablets in a tightly closed container at room temperature between 20° to 25°C (68° to 77°F).
- Keep lorazepam tablets and all medicines out of the reach of children.

General information about the safe and effective use of lorazepam tablets
Medicines are sometimes prescribed for purposes other than those listed in a Medication Guide. Do not use lorazepam tablets for a condition for which it was not prescribed. Do not give lorazepam tablets to other people, even if they have the same symptoms that you have. It may harm them. You can ask your pharmacist or healthcare provider for information about lorazepam tablets that is written for health professionals.

What are the ingredients in lorazepam tablets?
Active ingredient:lorazepam
Inactive ingredients:anhydrous lactose, magnesium stearate, microcrystalline cellulose, and polacrilin potassium.
Distributed by:
Aurobindo Pharma USA, Inc.
279 Princeton-Hightstown Road
East Windsor, NJ 08520
Manufactured by:
Aurobindo Pharma Limited
Hyderabad-500 032, India
For more information, call Aurobindo Pharma USA, Inc. at 1-866-850-2876.

This Medication Guide has been approved by the U.S. Food and Drug Administration.

Revised: 06/2023

PACKAGE LABEL-PRINCIPAL DISPLAY PANEL - 2 mg Label

Rx only
Lorazepam Tablets, USP
2 mg CIV
PHARMACIST: Dispense the Medication Guide
provided separately to each patient.